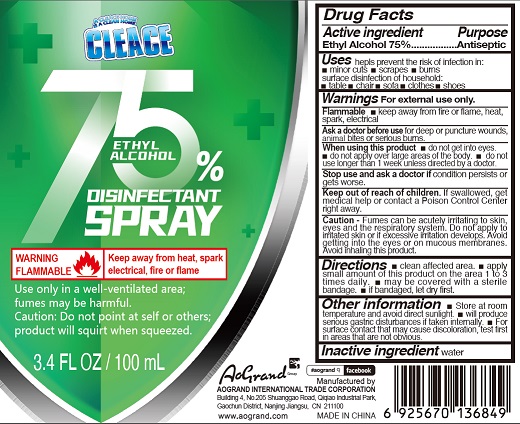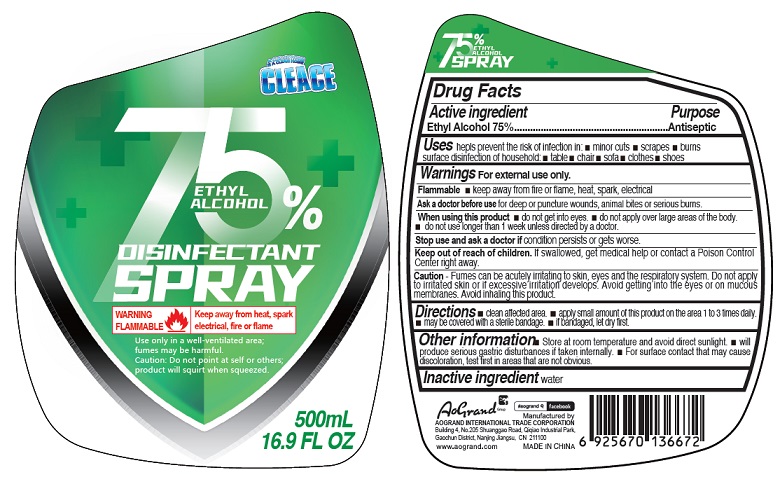 DRUG LABEL: Cleace disinfectant
NDC: 74621-027 | Form: LIQUID
Manufacturer: AOGRAND INTERNATIONAL TRADE CORPORATION
Category: otc | Type: HUMAN OTC DRUG LABEL
Date: 20200515

ACTIVE INGREDIENTS: ALCOHOL 70 mL/100 mL
INACTIVE INGREDIENTS: WATER

Active Ingredient

Ethyl Alcohol 75%

Purpose

Antiseptic

Uses

hepls prevent the risk of infection in: ■ minor cuts ■ scrapes ■ burns
surface disinfection of household: ■ Table ■ chair ■ sofa ■ clothes ■ shoes

Warnings

For external use only.
Flammable. ■ keep away from fire or flame, heat, spark, electrical
Ask a doctor before use for deep or puncture wounds, animal bites or serious burns.
When using this product ■ do not get into eyes. ■ do not apply over large areas of the body. ■ do not use longer than 1 week unless directed by a doctor.

Stop use and ask a doctor if condition persists or gets worse.

Caution - Fumes can be acutely irritating to skin, eyes and the respiratory system. Do not apply to irritated skin or if excessive irritation develops. Avoid getting into the eyes or on mucous membranes. Avoid inhaling this product.

Keep out of reach of children. If swallowed, get medical help or contact a Poison Control Center right away.

Directions

■ clean affected area.
■ apply small amount of this product on the area 1 to 3 times daily.
■ may be covered with a sterile bandage.
■ if bandaged, let dry first.

Other information
■ Store at room temperature and avoid direct sunlight.
■ will produce serious gastric disturbances if taken internally.
■ For surface contact that may cause discoloration, test first in areas that are not obvious.

Inactive ingredients

Water.

Package Label - Principal Display Panel

500 mL Label

1000 mL Label